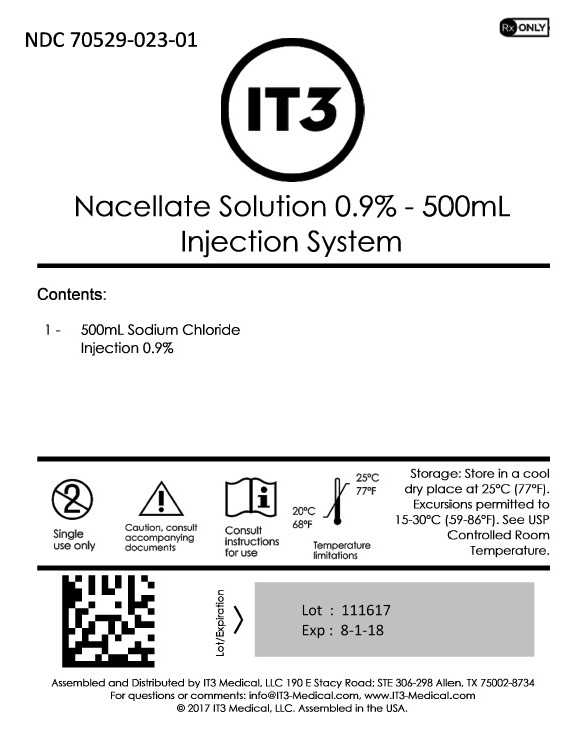 DRUG LABEL: Nacellate Solution 0.9% - 500mL
NDC: 70529-023 | Form: INJECTION, SOLUTION
Manufacturer: IT3 Medical LLC
Category: prescription | Type: HUMAN PRESCRIPTION DRUG LABEL
Date: 20220223

ACTIVE INGREDIENTS: SODIUM CHLORIDE 9 g/1000 mL
INACTIVE INGREDIENTS: WATER

Nacellate Solution 0.9% - 500mL

DESCRIPTION

Sodium Chloride Injection, USP is a sterile, nonpyrogenic solution for fluid and electrolyte replenishment in single dose containers for intravenous administration. It contains no antimicrobial agents. The nominal pH is 5.0 (4.5 to 7.0). Composition, osmolarity, and ionic concentration are shown below:

0.45% Sodium Chloride Injection, USP contains 4.5 g/L Sodium Chloride, USP (NaCl) and is hypotonic with an osmolarity of 154 mOsmol/L (calc). It contains 77 mEq/L sodium and 77 mEq/L chloride.

0.9% Sodium Chloride Injection, USP contains 9 g/L Sodium Chloride, USP (NaCl) with an osmolarity of 308 mOsmol/L (calc). It contains 154 mEq/L sodium and 154 mEq/L chloride.

The VIAFLEX plastic container is fabricated from a specially formulated polyvinyl chloride (PL 146 Plastic). The amount of water that can permeate from inside the container into the overwrap is insufficient to affect the solution significantly. Solutions in contact with the plastic container can leach out certain of its chemical components in very small amounts within the expiration period, e.g., di-2-ethylhexyl phthalate (DEHP), up to 5 parts per million. However, the safety of the plastic has been confirmed in tests in animals according to USP biological tests for plastic containers as well as by tissue culture toxicity studies.

CLINICAL PHARMACOLOGY

Sodium Chloride Injection, USP has value as a source of water and electrolytes. It is capable of inducing diuresis depending on the clinical condition of the patient.

INDICATIONS AND USAGE

Sodium Chloride Injection, USP is indicated as a source of water and electrolytes.

0.9% Sodium Chloride Injection, USP is also indicated for use as a priming solution in hemodialysis procedures.

CONTRAINDICATIONS

None known.

WARNINGS

Hypersensitivity/infusion reactions, including hypotension, pyrexia, tremor, chills, urticaria, rash, and pruritus have been reported with 0.9% Sodium Chloride Injection, USP and may occur with 0.45% Sodium Chloride Injection, USP.

Stop the infusion immediately if signs or symptoms of a hypersensitivity reaction develop, such as tachycardia, chest pain, dyspnea and flushing. Appropriate therapeutic countermeasures must be instituted as clinically indicated.

Depending on the volume and rate of infusion, the intravenous administration of Sodium Chloride Injection, USP can cause fluid and/or solute overloading resulting in dilution of serum electrolyte concentrations, overhydration/hypervolemia, congested states, pulmonary edema, or acid-base imbalance. The risk of dilutive states is inversely proportional to the electrolyte concentration of the injection. The risk of solute overload causing congested states with peripheral and pulmonary edema is directly proportional to the electrolyte concentrations of the injection.

Monitor changes in fluid balance, electrolyte concentrations, and acid base balance during prolonged parenteral therapy or whenever the condition of the patient or the rate of administration warrants such evaluation.

Administer 0.9% Sodium Chloride Injection, USP with particular caution, to patients with or at risk for hypernatremia, hyperchloremia, or metabolic acidosis.

The infusion of solutions with 0.45% Sodium Chloride Injection, USP may result in hyponatremia. Close clinical monitoring may be warranted. Hyponatremia can lead to headache, nausea, seizures, lethargy, coma, cerebral edema and death. The risk for hyponatremia is increased, for example, in children, elderly, women, postoperatively, in persons with psychogenic polydipsia, and in patients treated with medications that increase the risk of hyponatremia (such as certain antiepileptic and psychotropic medications). The risk for developing hyponatremic encephalopathy is increased, for example, in pediatric patients (≤16 years of age), women (in particular pre-menopausal women), in patients with hypoxemia, and in patients with underlying central nervous system disease. Acute symptomatic hyponatremic encephalopathy is considered a medical emergency.

Administer Sodium Chloride Injection, USP with particular caution, to patients with or at risk for hypervolemia or with conditions that may cause sodium retention, fluid overload and edema; such as patients with primary hyperaldosteronism, or secondary hyperaldosteronism [e.g., associated with hypertension, congestive heart failure, liver disease (including cirrhosis), renal disease (including renal artery stenosis, nephrosclerosis) or pre-eclampsia]. Certain medications may increase risk of sodium and fluid retention, see Drug Interactions.

Administer Sodium Chloride Injection, USP with particular caution, to patients with severe renal impairment. In such patients, administration of Sodium Chloride Injection, USP may result in sodium retention.

PRECAUTIONS

General

Do not connect flexible plastic containers in series in order to avoid air embolism due to possible residual air contained in the primary container. Such use could result in air embolism due to residual air being drawn from the primary container before administration of the fluid from the secondary container is completed.

Pressurizing intravenous solutions contained in flexible plastic containers to increase flow rates can result in air embolism if the residual air in the container is not fully evacuated prior to administration.

Use of a vented intravenous administration set with the vent in the open position could result in air embolism. Vented intravenous administration sets with the vent in the open position should not be used with flexible plastic containers.

Do not mix or administer 0.45% Sodium Chloride Injection, USP through the same administration set with whole blood or cellular blood components.

Rapid correction of hypo- and hypernatremia is potentially dangerous (risk of serious neurologic complications). Dosage, rate, and duration of administration should be determined by a physician experienced in intravenous fluid therapy.

Drug Interactions

Caution must be exercised in the administration of Sodium Chloride Injection, USP to patients treated with drugs that may increase the risk of sodium and fluid retention, such as corticosteroids.

Caution is advised in patients treated with lithium. Renal sodium and lithium clearance may be decreased in the presence of hyponatremia. Administration of 0.45% Sodium Chloride Injection, USP may result in increased lithium levels.

Renal sodium and lithium clearance may be increased during administration of 0.9% Sodium Chloride Injection, USP. Administration of 0.9% Sodium Chloride Injection, USP, may result in decreased lithium levels.

Pregnancy

There are no adequate and well controlled studies with Sodium Chloride Injection, USP in pregnant women and animal reproduction studies have not been conducted with this drug. Therefore, it is not known whether Sodium Chloride Injection, USP can cause fetal harm when administered to a pregnant woman. Sodium Chloride Injection, USP should be given to a during pregnancy only if the potential benefit justifies the potential risk to the fetus.

Nursing Mothers

It is not known whether this drug is present in human milk. Because many drugs are present in human milk, caution should be exercised when Sodium Chloride Injection, USP is administered to a nursing woman.

Pediatric Use

The use of Sodium Chloride Injection, USP in pediatric patients is based on clinical practice. (See DOSAGE AND ADMINISTRATION).

Plasma electrolyte concentrations should be closely monitored in the pediatric population as this population may have impaired ability to regulate fluids and electrolytes.

The infusion of hypotonic fluids (0.45% Sodium Chloride Injection, USP) together with the non-osmotic secretion of ADH may result in hyponatremia in patients with acute volume depletion. Hyponatremia can lead to headache, nausea, seizures, lethargy, coma, cerebral edema and death, therefore acute symptomatic hyponatremic encephalopathy is considered a medical emergency.

Geriatric Use

Clinical studies of Sodium Chloride Injection, USP did not include sufficient numbers of subjects aged 65 and over to determine whether they respond differently from younger subjects. Other reported clinical experience has not identified differences in responses between the elderly and younger patients. In general, dose selection for an elderly patient should be cautious, usually starting at the low end of the dosing range, reflecting the greater frequency of decreased hepatic, renal, or cardiac function, and of concomitant disease or other drug therapy.

This drug is known to be substantially excreted by the kidney, and the risk of toxic reactions to this drug may be greater in patients with impaired renal function. Because elderly patients are more likely to have decreased renal function, care should be taken in dose selection, and it may be useful to monitor renal function.

ADVERSE REACTIONS

Post-Marketing Adverse Reactions

The following adverse reactions have been identified during postapproval use of Sodium Chloride Injection, USP. Because these reactions are reported voluntarily from a population of uncertain size, it is not always possible to reliably estimate their frequency or establish a causal relationship to drug exposure.

The following adverse reactions have been reported in the post-marketing experience during use of 0.9% Sodium Chloride Injection, USP and include the following:

hypersensitivity/infusion reactions, including hypotension, pyrexia, tremor, chills, urticaria, rash, and pruritus.

Also reported are infusion site reactions, such as infusion site erythema, injection site streaking, burning sensation, and infusion site urticaria.

The following adverse reactions have not been reported with 0.9% Sodium Chloride Injection, USP but may occur: hypernatremia, hyperchloremic metabolic acidosis, and hyponatremia, which may be symptomatic.

Hyponatremia has been reported for 0.45% Sodium Chloride Injection, USP (see Pediatric Use section).

The following adverse reactions have not been reported with 0.45% Sodium Chloride Injection, USP but may occur: hyperchloremic metabolic acidosis, hypersensitivity/infusion reactions (including hypotension, pyrexia, tremor, chills, urticaria, rash, and pruritus), and infusion site reactions (such as infusion site erythema, injection site streaking, burning sensation, infusion site urticaria).

If an adverse reaction does occur, discontinue the infusion, evaluate the patient, institute appropriate therapeutic countermeasures and save the remainder of the fluid for examination if deemed necessary.

OVERDOSAGE

Excessive administration of 0.45% Sodium Chloride Injection, USP may lead to hypo- and hypernatremia, while excessive administration of 0.9% Sodium Chloride Injection, USP may lead to hypernatremia. Both hypo- and hypernatremia can lead to CNS manifestations, including seizures, coma, cerebral edema and death.

Excessive administration of Sodium Chloride Injection, USP may lead to sodium overload (which can lead to central and/or peripheral edema).

When assessing an overdose, any additives in the solution must also be considered. The effects of an overdose may require immediate medical attention and treatment.

DOSAGE AND ADMINISTRATION

All injections in VIAFLEX plastic containers are intended for intravenous administration using sterile and nonpyrogenic equipment.

As directed by a physician. Dosage, rate, and duration of administration are to be individualized and depend upon the indication for use, the patient’s age, weight, clinical condition, concomitant treatment, and on the patient’s clinical and laboratory response to treatment.

When other electrolytes or medicines are added to this solution, the dosage and the infusion rate will also be dictated by the dose regimen of the additions.

Parenteral drug products should be inspected visually for particulate matter and discoloration prior to administration whenever solution and container permit. Use of a final filter is recommended during administration of all parenteral solutions, where possible.

Do not administer unless the solution is clear and seal is intact.

Additives may be incompatible with Sodium Chloride Injection, USP. As with all parenteral solutions, compatibility of the additives with the solution must be assessed before addition. Before adding a substance or medication, verify that it is soluble and/or stable in water and that the pH range of Sodium Chloride Injection, USP is appropriate. After addition, check for unexpected color changes and/or the appearance of precipitates, insoluble complexes or crystals.

The instructions for use of the medication to be added and other relevant literature must be consulted. Additives known or determined to be incompatible must not be used. When introducing additives to Sodium Chloride Injection, USP, aseptic technique must be used. Mix the solution thoroughly when additives have been introduced. Do not store solutions containing additives.

After opening the container, the contents should be used immediately and should not be stored for a subsequent infusion. Do not reconnect any partially used containers. Discard any unused portion.

HOW SUPPLIED

The available sizes of each injection in VIAFLEX plastic containers are shown below:

Code | Size (mL) | NDC | Product Name
2B1323 | 500 | 70529-023-01

Exposure of pharmaceutical products to heat should be minimized. Avoid excessive heat. It is recommended the product be stored at room temperature (25°C/77°F); brief exposure up to 40°C/104°F does not adversely affect the product.

DIRECTIONS FOR USE OF VIAFLEX PLASTIC CONTAINER

For Information on Risk of Air Embolism – see PRECAUTIONS.

To Open

Tear overwrap down side at slit and remove solution container. Visually inspect the container. If the outlet port protector is damaged, detached, or not present, discard container as solution path sterility may be impaired. Some opacity of the plastic due to moisture absorption during the sterilization process may be observed. This is normal and does not affect the solution quality or safety. The opacity will diminish gradually. Check for minute leaks by squeezing inner bag firmly. If leaks are found, discard solution as sterility may be impaired. If supplemental medication is desired, follow directions below.

Preparation for Administration

1. Suspend container from eyelet support.
2. Remove protector from outlet port at bottom of container.
3. Attach administration set. Refer to complete directions accompanying set.

To Add Medication

Additives may be incompatible

To add medication before solution administration

1. Prepare medication site.
2. Using syringe with 19 to 22 gauge needle, puncture resealable medication port and inject.
3. Mix solution and medication thoroughly. For high density medication such as potassium chloride, squeeze ports while ports are upright and mix thoroughly.

To add medication during solution administration

1. Close clamp on the set.
2. Prepare medication site.
3. Using syringe with 19 to 22 gauge needle, puncture resealable medication port and inject.
4. Remove container from IV pole and/or turn to an upright position.
5. Evacuate both ports by squeezing them while container is in the upright position.
6. Mix solution and medication thoroughly.
7. Return container to in-use position and continue administration.

07-19-00-0278

Rev. March 2018

Assembled and Distributed by IT3 Medical, LLC 190 E Stacy Road; STE 306-298, Allen, TX 75002-8734
For questions or comments: info@IT3-Medical.com, www.IT3-Medical.com